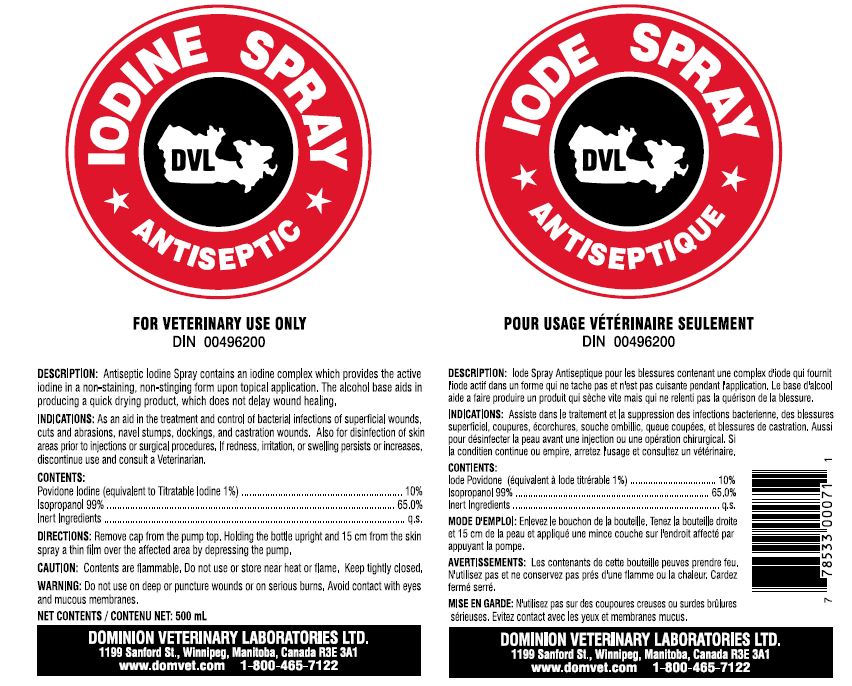 DRUG LABEL: IODINE
NDC: 64120-105 | Form: SPRAY
Manufacturer: DOMINION VETERINARY LABORATORIES LTD.
Category: animal | Type: OTC ANIMAL DRUG LABEL
Date: 20211110

ACTIVE INGREDIENTS: POVIDONE-IODINE 10 g/100 mL
INACTIVE INGREDIENTS: ISOPROPYL ALCOHOL 65 mL/100 mL

DOMINION VETERINARY LABORATORIES - IODINE SPRAY ANTISEPTIC

INDICATIONS:

AS AN AID IN THE TREATMENT AND CONTROL OF BACTERIAL INFECTIONS OF SUPERFICIAL WOUNDS, CUTS AND ABRASIONS, NAVAL STAMPS, DOCKINGS, AND CASTRATION WOUNDS. ALSO FOR DISINFECTION OF SKIN AREAS PRIOR TO INJECTIONS OR SURGICAL PROCEDURES. IF REDNESS, IRRITATION, OR SWELLING PERSISTS OR INCREASES, DISCONTINUE USE AND CONSULT A VETERINARIAN.